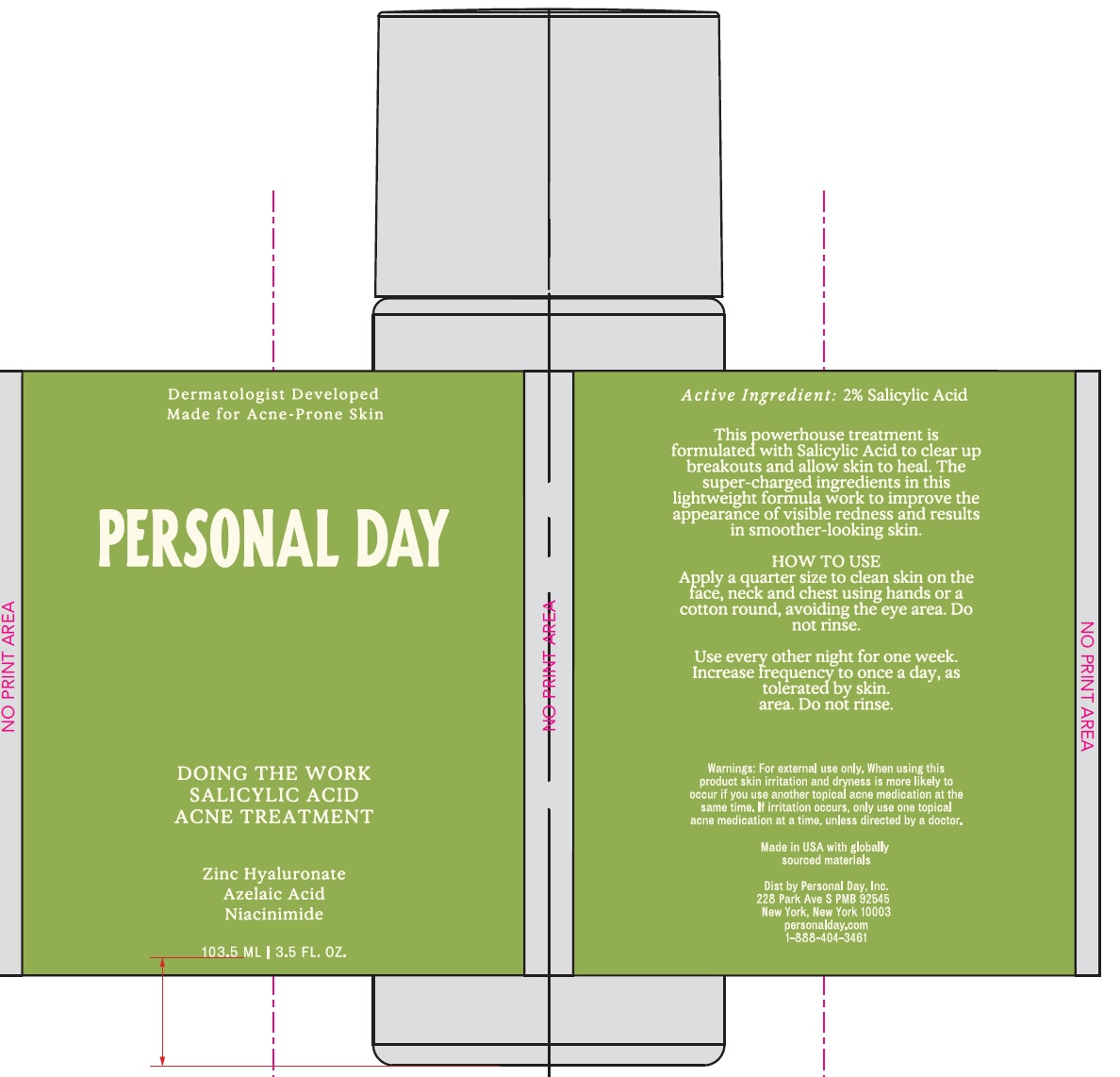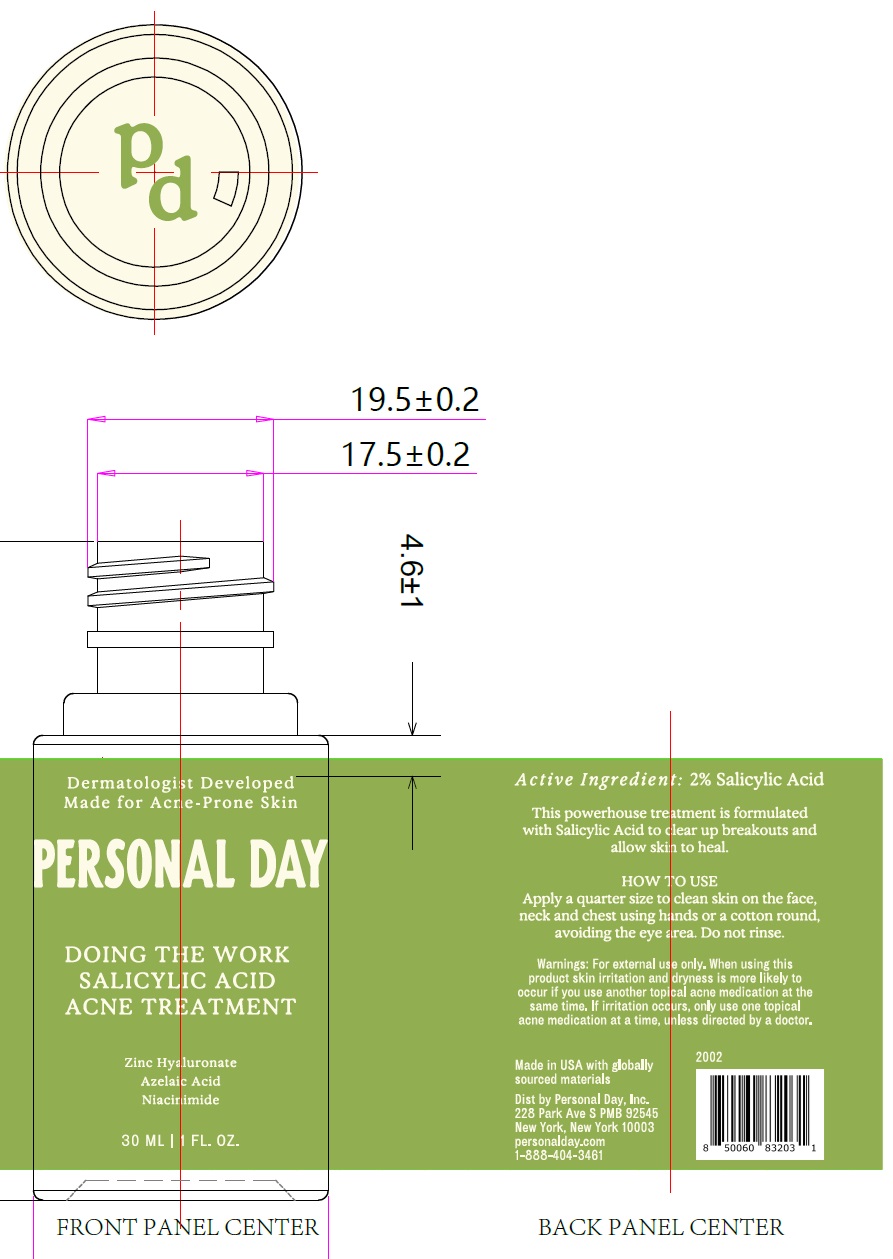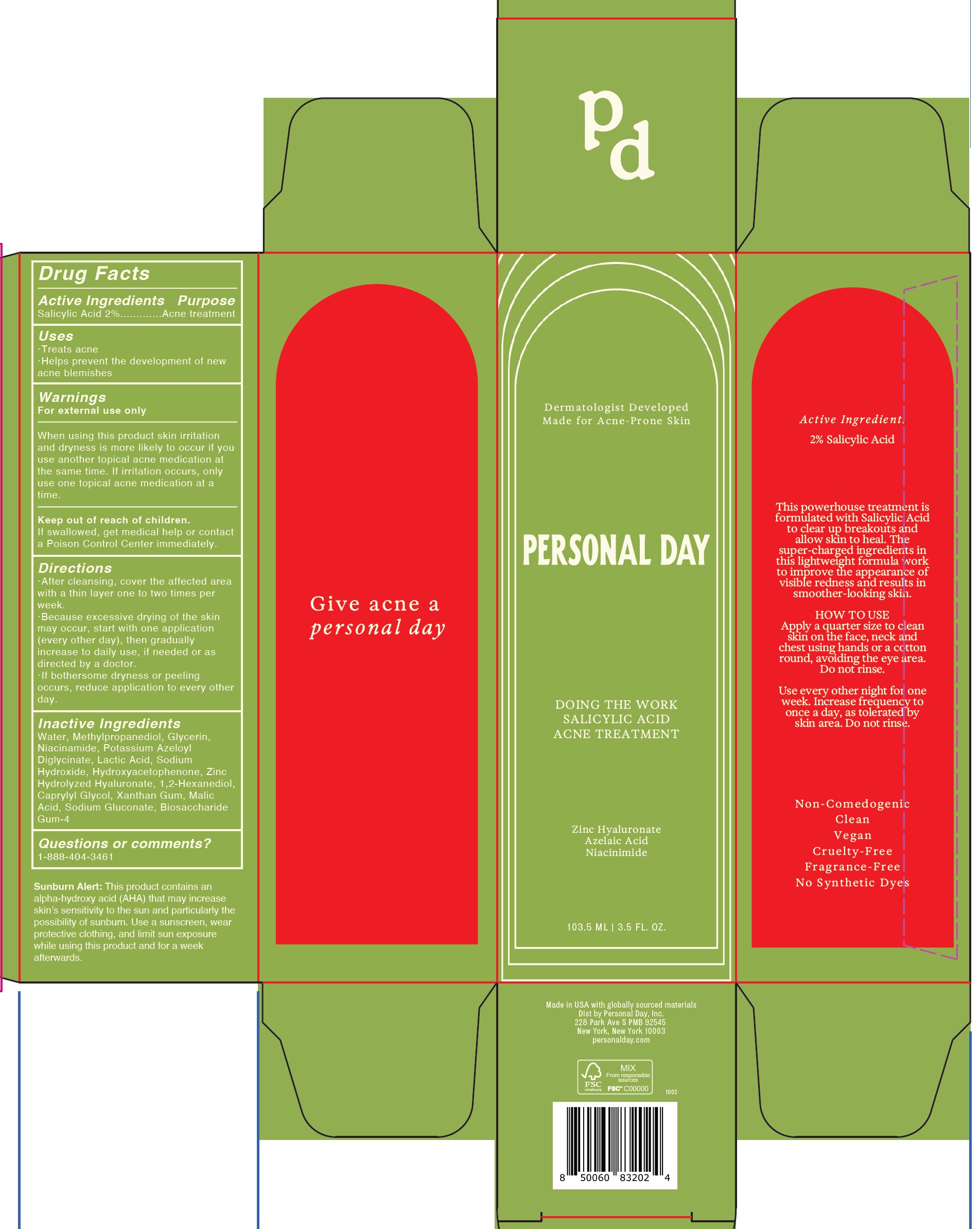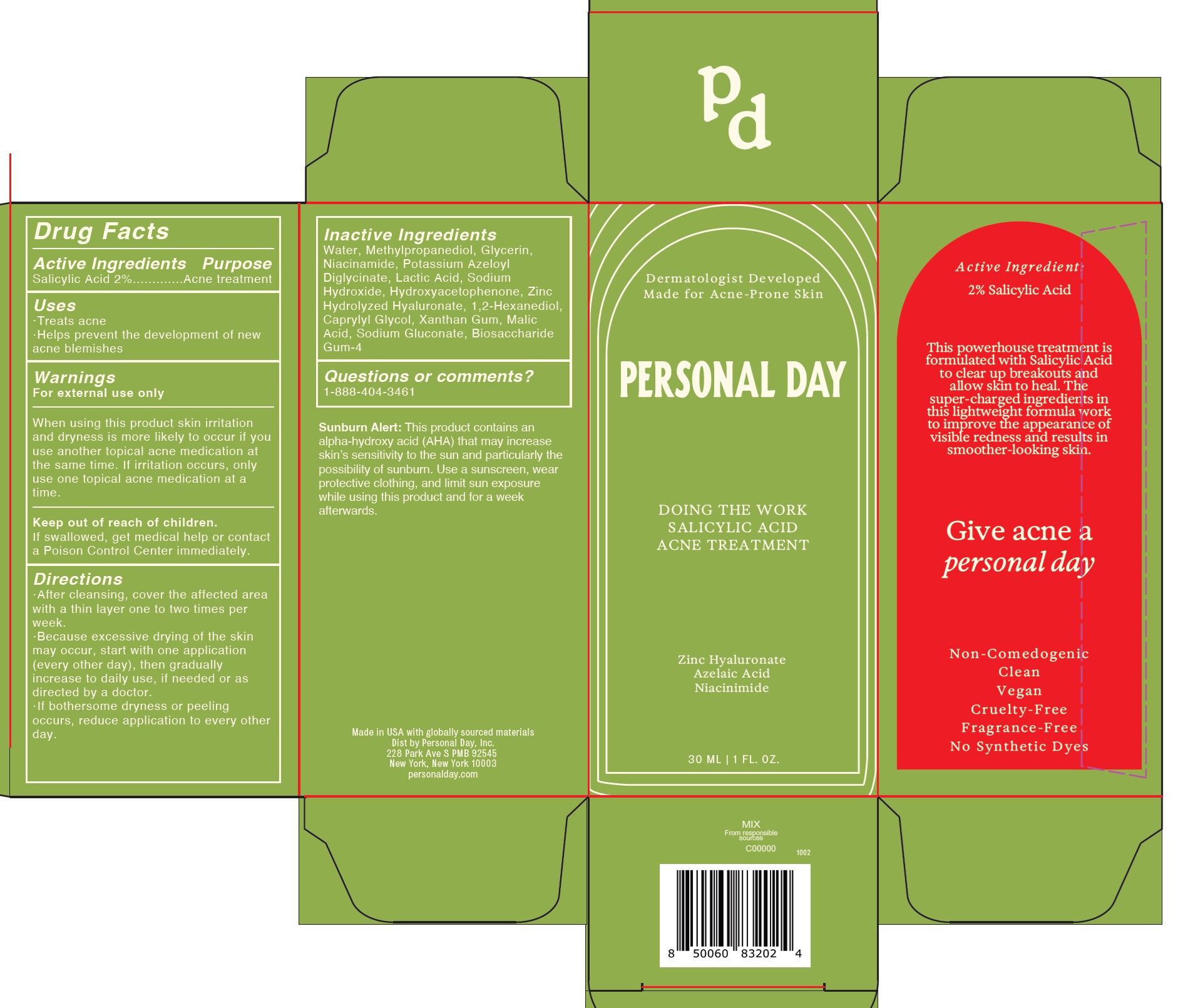 DRUG LABEL: DOING THE WORK SALICYLIC ACID ACNE TREATMENT
NDC: 84234-001 | Form: LIQUID
Manufacturer: Personal Day Inc.
Category: otc | Type: HUMAN OTC DRUG LABEL
Date: 20241125

ACTIVE INGREDIENTS: SALICYLIC ACID 20 mg/1 mL
INACTIVE INGREDIENTS: WATER; METHYLPROPANEDIOL; GLYCERIN; NIACINAMIDE; POTASSIUM AZELOYL DIGLYCINATE; LACTIC ACID; SODIUM HYDROXIDE; HYDROXYACETOPHENONE; 1,2-HEXANEDIOL; CAPRYLYL GLYCOL; XANTHAN GUM; MALIC ACID; SODIUM GLUCONATE; BIOSACCHARIDE GUM-4

DOING THE WORK SALICYLIC ACID ACNE TREATMENT

Active Ingredients

Salicylic Acid 2%

Purpose

Acne treatment

Uses

- Treats acne
- Helps prevent the development of new acne blemishes

Warnings

For external use only

When using this product

skin irritation and dryness is more likely to occur if you use another topical acne medication at the same time. If irritation occurs, only use one topical acne medication at a time.

Keep out of reach of children.

If swallowed, get medical help or contact a Poison Control Center immediately.

Directions

- After cleansing, cover the affected area with a thin layer one to two times per week.
- Because excessive drying of the skin may occur, start with one application (every other day), then gradually increase to two times weekly, if needed or as directed by a doctor.
- If bothersome dryness or peeling occurs, reduce application to every other week.

Inactive Ingredients

Water, Methylpropanediol, Glycerin, Niacinamide, Potassium Azeloyl Diglycinate, Lactic Acid, Sodium Hydroxide, Hydroxyacetophenone, Zinc Hydrolyzed Hyaluronate, 1,2-Hexanediol, Caprylyl Glycol, Xanthan Gum, Malic Acid, Sodium Gluconate, Biosaccharide Gum-4

Questions or comments?

1-888-404-3461